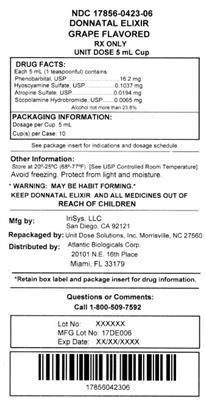 DRUG LABEL: Donnatal
                                    
NDC: 17856-0423 | Form: ELIXIR
Manufacturer: Atlantic Biologicals Corps
Category: prescription | Type: HUMAN PRESCRIPTION DRUG LABEL
Date: 20180510
DEA Schedule: CIV

ACTIVE INGREDIENTS: PHENOBARBITAL 16.2 mg/5 mL; HYOSCYAMINE SULFATE 0.1037 mg/5 mL; SCOPOLAMINE HYDROBROMIDE 0.0065 mg/5 mL; ATROPINE SULFATE 0.0194 mg/5 mL
INACTIVE INGREDIENTS: GLYCERIN 2.007 g/5 mL; ALCOHOL 0.4158 g/5 mL; WATER 2.1432 g/5 mL; sucrose .2925 g/5 mL; sorbitol .9068 g/5 mL; saccharin sodium .02925 g/5 mL; FD&C Blue No. 1; FD&C Red No. 3; GRAPE 0.041 g/5 mL

DONNATAL ELIXIR grape flavor 1 pint

DESCRIPTION

Each Donnatal(r) 5 mL (teaspoonful) of elixir (alcohol not more than 23.8%) contains:

Phenobarbital, USP....................................... 16.2 mg

Hyoscyamine Sulfate, USP...................... 0.1037 mg

Atropine Sulfate, USP ...............................0.0194 mg

Scopolamine Hydrobromide, USP ...........0.0065 mg

INACTIVE INGREDIENTS: Artificial Grape Flavor, FD and C Blue #1, FD and C Red #3, Ethyl Alcohol, Glycerin, Purified Water, Saccharin Sodium, Sorbitol, and Sucrose.

CLINICAL PHARMACOLOGY

This drug combination provides natural belladonna alkaloids in a specific, fixed ratio combined with phenobarbital to provide peripheral anticholinergic/antispasmodic action and mild sedation.

INDICATIONS & USAGE

Based on a review of this drug by the National Academy of Sciences-National Research Council and/or other information, FDA has classified the following indications as “possibly” effective: For use as adjunctive therapy in the treatment of irritable bowel syndrome (irritable colon, spastic colon, mucous colitis) and acute enterocolitis. May also be useful as adjunctive therapy in the treatment of duodenal ulcer. IT HAS NOT BEEN SHOWN CONCLUSIVELY WHETHER ANTICHOLINERGIC/ANTISPASMODIC DRUGS AID IN THE HEALING OF A DUODENAL ULCER, DECREASE THE RATE OF RECURRENCES OR PREVENT COMPLICATIONS.

CONTRAINDICATIONS

Glaucoma, obstructive uropathy (for example, bladder neck obstruction due to prostatic hypertrophy); obstructive disease of the gastrointestinal tract (as in achalasia, pyloroduodenal stenosis, etc.); paralytic ileus, intestinal atony of the elderly or debilitated patient; unstable cardiovascular status in acute hemorrhage; severe ulcerative colitis especially if complicated by toxic megacolon; myasthenia gravis; hiatal hernia associated with reflux esophagitis.

Donnatal® Elixir is contraindicated in patients with known hypersensitivity to any of the ingredients. Phenobarbital is contraindicated in acute intermittent porphyria and in those patients in whom Phenobarbital produces restlessness and/or excitement.

WARNINGS

In the presence of a high environmental temperature, heat prostration can occur with belladonna alkaloids (fever and heatstroke due to decreased sweating).

Diarrhea may be an early symptom of incomplete intestinal obstruction, especially in patients with ileostomy or colostomy. In this instance, treatment with this drug would be inappropriate and possibly harmful.

Donnatal® Elixir may produce drowsiness or blurred vision. The patient should be warned, should these occur, not to engage in activities requiring mental alertness, such as operating a motor vehicle or other machinery, and not to perform hazardous work.

Phenobarbital may decrease the effect of anticoagulants, and necessitate larger doses of the anticoagulant for optimal effect. When the phenobarbital is discontinued, the dose of the anticoagulant may have to be decreased.

Phenobarbital may be habit forming and should not be administered to individuals known to be addiction prone or to those with a history of physical and/or psychological dependence upon drugs.

Since barbiturates are metabolized in the liver, they should be used with caution and initial doses should be small in patients with hepatic dysfunction.

PRECAUTIONS

GENERAL

Use with caution in patients with: autonomic neuropathy, hepatic or renal disease, hyperthyroidism, coronary heart disease, congestive heart failure, cardiac arrhythmias, tachycardia, and hypertension.

Belladonna alkaloids may produce a delay in gastric emptying (antral stasis) which would complicate the management of gastric ulcer.

Do not rely on the use of the drug in the presence of complication of biliary tract disease. Theoretically, with overdosage, a curare-like action may occur.

CARCINOGENESIS, MUTAGENESIS, IMPAIRMENT OF FERTILITY: Long-term studies in animals have not been performed to evaluate carcinogenic potential.

PREGNANCY

PREGNANCY CATEGORY C

Animal reproduction studies have not been conducted with Donnatal® Elixir. It is not known whether Donnatal®

Elixir can cause fetal harm when administered to a pregnant woman or can affect reproduction capacity. Donnatal® Elixir should be given to a pregnant woman only if clearly needed.

NURSING MOTHERS. It is not known whether this drug is excreted in human milk. Because many drugs are excreted in human milk, caution should be exercised when Donnatal® Elixir is administered to a nursing woman.

ADVERSE REACTIONS

Adverse reactions may include xerostomia; urinary hesitancy and retention; blurred vision; tachycardia; palpitation; mydriasis; cycloplegia; increased ocular tension; loss of taste sense; headache; nervousness; drowsiness; weakness; dizziness; insomnia; nausea; vomiting; impotence; suppression of lactation; constipation; bloated feeling; musculoskeletal pain; severe allergic reaction or drug idiosyncrasies, including anaphylaxis, urticaria and other dermal manifestations; and decreased sweating. Elderly patients may react with symptoms of excitement, agitation, drowsiness, and other untoward manifestations to even small doses of the drug. Phenobarbital may produce excitement in some patients, rather than a sedative effect. In patients habituated to barbiturates, abrupt withdrawal may produce delirium or convulsions.

OVERDOSAGE

The signs and symptoms of overdose are headache, nausea, vomiting, blurred vision, dilated pupils, hot and dry skin, dizziness, dryness of the mouth, difficulty in swallowing, and CNS stimulation. Treatment should consist of gastric lavage, emetics, and activated charcoal. If indicated, parenteral cholinergic agents such as physostigmine or bethanechol chloride, should be used.

DOSAGE & ADMINISTRATION

The dosage of Donnatal® Elixir should be adjusted to the needs of the individual patient to assure symptomatic control with a minimum of adverse effects.

Donnatal® Elixir. Adults: One or two teaspoonfuls of elixir three or four times a day according to conditions and severity of symptoms.

Pediatric patients: may be dosed every 4 to 6 hours.

Starting dosage

Body weight q4h q6h

10 lb. (4.5 kg) 0.5 mL 0.75 mL

20 lb. (9.1 kg) 1.0 mL 1.5 mL

30 lb. (13.6 kg) 1.5 mL 2.0 mL

50 lb. (22.7 kg) ½ tsp ¾ tsp

75 lb. (34 kg) ¾ tsp 1 tsp

100 lb. (45.4 kg) 1 tsp 1½ tsp

STORAGE CONDITIONS

Product: 17856-0423

NDC: 17856-0423-3 10 mL in a CUP

NDC: 17856-0423-5 5 mL in a CUP

NDC: 17856-0423-2 15 mL in a CUP

NDC: 17856-0423-4 5 mL in a CUP

NDC: 17856-0423-6 5 mL in a CUP / 10 in a CASE

NDC: 17856-0423-8 15 mL in a CUP

NDC: 17856-0423-9 10 mL in a CUP